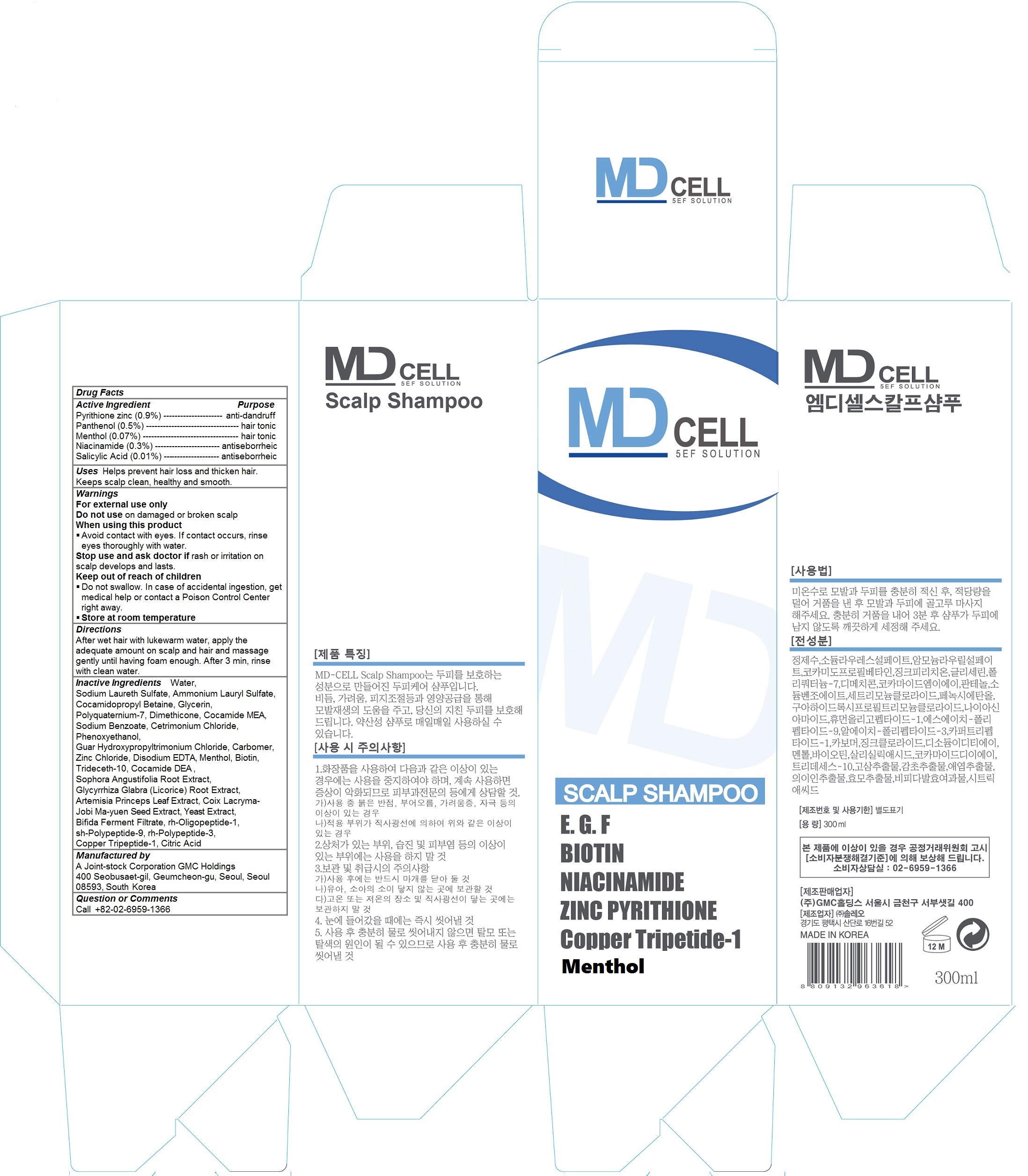 DRUG LABEL: MD CELL Scalp
NDC: 70834-101 | Form: SHAMPOO
Manufacturer: A Joint-stock Corporation GMC Holdings
Category: otc | Type: HUMAN OTC DRUG LABEL
Date: 20160826

ACTIVE INGREDIENTS: Pyrithione zinc 2.7 g/300 mL; Panthenol 1.5 g/300 mL; Niacinamide 0.9 g/300 mL; Menthol 0.21 g/300 mL; Salicylic Acid 0.03 g/300 mL
INACTIVE INGREDIENTS: water; SODIUM LAURETH-3 SULFATE; Ammonium Lauryl Sulfate; Cocamidopropyl Betaine; Glycerin; POLYQUATERNIUM-7 (70/30 ACRYLAMIDE/DADMAC; 1600000 MW); Dimethicone; COCO MONOETHANOLAMIDE; Sodium Benzoate; Cetrimonium Chloride; Phenoxyethanol; GUAR HYDROXYPROPYLTRIMONIUM CHLORIDE (1.7 SUBSTITUENTS PER SACCHARIDE); CARBOXYPOLYMETHYLENE; Zinc Chloride; EDETATE DISODIUM; Biotin; Trideceth-10; COCO DIETHANOLAMIDE; SOPHORA FLAVESCENS ROOT; GLYCYRRHIZA GLABRA; ARTEMISIA PRINCEPS LEAF; COIX LACRYMA-JOBI VAR. MA-YUEN SEED; YEAST, UNSPECIFIED; NEPIDERMIN; FIBROBLAST GROWTH FACTOR 7; PREZATIDE COPPER; CITRIC ACID MONOHYDRATE

MD CELL Scalp Shampoo

Active ingredients

Pyrithione zinc (0.9%)

Panthenol (0.5%)

Niacinamide (0.3%)

Salicylic Acid (0.01%)

PURPOSE

anti-dandruff

hair tonic

antiseborrheic

Keep out of reach of children

Do not swallow. In case of accidental ingestion, get medical help or contact a Poison Control Center right away.

Uses

Helps prevent hair loss and thicken hair. Keeps scalp clean, healthy and smooth.

Warnings

For external use only
Do not use on damaged or broken scalp
When using this product
- Avoid contact with eyes. If contact occurs, rinse eyes thoroughly with water.
Stop use and ask doctor if rash or irritation on scalp develops and lasts.

Store at room temperature

Directions

After wet hair with lukewarm water, apply the adequate amount on scalp and hair and massage gently until having foam enough. After 3 min, rinse with clean water.

Inactive Ingredients

Water, Sodium Laureth Sulfate, Ammonium Lauryl Sulfate, Cocamidopropyl Betaine, Glycerin, Polyquaternium-7, Dimethicone, Cocamide MEA, Sodium Benzoate, Cetrimonium Chloride, Phenoxyethanol, Guar Hydroxypropyltrimonium Chloride, Carbomer, Zinc Chloride, Disodium EDTA, Menthol, Biotin, Trideceth-10, Cocamide DEA , Sophora Angustifolia Root Extract, Glycyrrhiza Glabra (Licorice) Root Extract, Artemisia Princeps Leaf Extract, Coix Lacryma-Jobi Ma-yuen Seed Extract, Yeast Extract, Bifida Ferment Filtrate, rh-Oligopeptide-1, sh-Polypeptide-9, rh-Polypeptide-3, Copper Tripeptide-1, Citric Acid